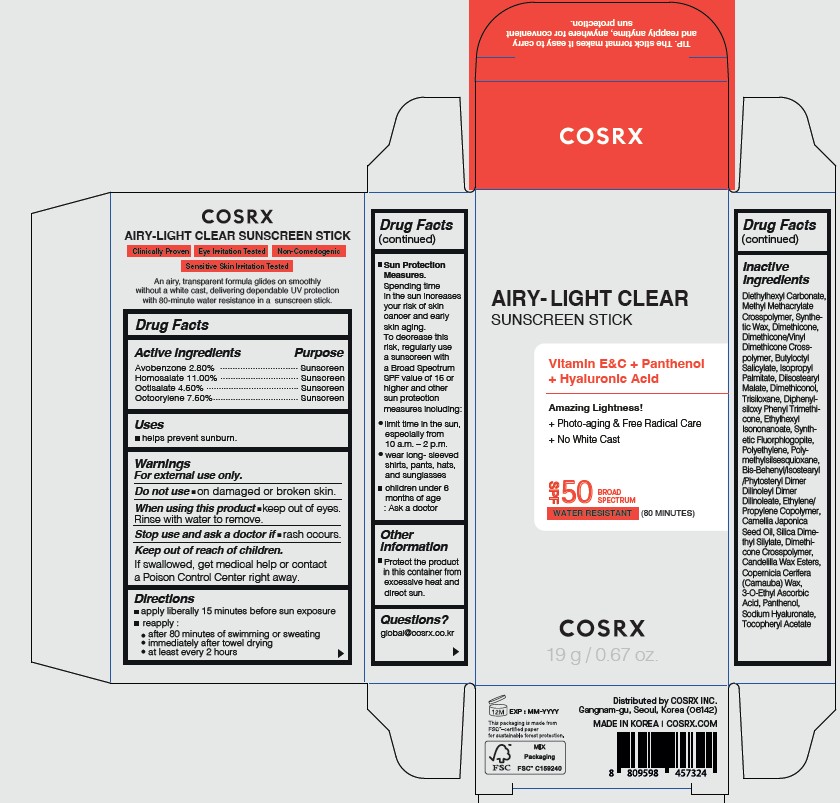 DRUG LABEL: COSRX
NDC: 70319-230 | Form: STICK
Manufacturer: COSRX inc.
Category: otc | Type: HUMAN OTC DRUG LABEL
Date: 20250520

ACTIVE INGREDIENTS: OCTISALATE 4.5 g/100 g; OCTOCRYLENE 7.5 g/100 g; AVOBENZONE 2.8 g/100 g; HOMOSALATE 11 g/100 g
INACTIVE INGREDIENTS: BUTYLOCTYL SALICYLATE; 3-O-ETHYL ASCORBIC ACID; SODIUM HYALURONATE; ALPHA-TOCOPHEROL ACETATE; PANTHENOL; DIETHYLHEXYL CARBONATE; POLYMETHYLSILSESQUIOXANE (4.5 MICRONS); ETHYLHEXYL ISONONANOATE; DIISOSTEARYL MALATE; TRISILOXANE; MAGNESIUM POTASSIUM ALUMINOSILICATE FLUORIDE; METHYL METHACRYLATE/GLYCOL DIMETHACRYLATE CROSSPOLYMER; BIS-BEHENYL/ISOSTEARYL/PHYTOSTERYL DIMER DILINOLEYL DIMER DILINOLEATE; DIMETHICONE; SILICA DIMETHYL SILYLATE; DIPHENYLSILOXY PHENYL TRIMETHICONE; COPERNICIA CERIFERA (CARNAUBA) WAX; ISOPROPYL PALMITATE; CAMELLIA JAPONICA SEED OIL; DIMETHICONE CROSSPOLYMER; POLYETHYLENE

ACTIVE INGREDIENT

Avobenzone 2.80%

Homosalate 11.00%

Octisalate 4.50%

Octocrylene 7.50%

PURPOSE

SUNSCREEN STICK

WHEN USING

helps prevent sunburn.

WARNINGS

For external use only.
Do not use on damaged or broken skin.
When using this product keep out of eyes. Rinse with water to remove.
Stop use and ask a doctor if rash occurs.

KEEP OUT OF REACH OF CHILDREN

If swallowed, get medical help or contact a Poison Control Center right away.

DESCRIPTION

apply liberally 15 minutes before sun exposure
reapply :
after 80 minutes of swimming or sweating

immediately after towel drying

at least every 2 hours

Sun Protection Measures. Spending time in the sun increases your risk of skin cancer and early skin aging.
To decrease this risk, regularly use a sunscreen with a Broad Spectrum SPF value of 15 or higher and other sun protection measures including:
limit time in the sun, especially from 10 a.m. – 2 p.m.
wear long- sleeved shirts, pants, hats, and sunglasses

children under 6 months of age : Ask a doctor

OTHER SAFETY INFORMATION

Protect the product in this container from excessive heat and direct sun.

INACTIVE INGREDIENT

Diethylhexyl Carbonate, Methyl Methacrylate Crosspolymer, Synthetic Wax, Dimethicone, Dimethicone/Vinyl Dimethicone Crosspolymer, Butyloctyl Salicylate, Isopropyl Palmitate, Diisostearyl Malate, Dimethiconol, Trisiloxane, Diphenylsiloxy Phenyl Trimethicone, Ethylhexyl Isononanoate, Synthetic Fluorphlogopite, Polyethylene, Polymethylsilsesquioxane, Bis-Behenyl/Isostearyl /Phytosteryl Dimer Dilinoleyl Dimer Dilinoleate, Ethylene/Propylene Copolymer, Camellia Japonica Seed Oil, Silica Dimethyl Silylate, Dimethicone Crosspolymer, Candelilla Wax Esters, Copernicia Cerifera (Carnauba) Wax, 3-O-Ethyl Ascorbic Acid, Panthenol, Sodium Hyaluronate, Tocopheryl Acetate

QUESTIONS

global@cosrx.co.kr

PACKAGE LABEL

AIRY-LIGHT CLEAR
SUNSCREEN STICK

Vitamin E&C + Panthenol
+ Hyaluronic Acid

Amazing Lightness!
+ Photo-aging & Free Radical Care
+ No White Cast

SPF50 BROAD SPECTRUM

WATER RESISTANT (80 MINUTES)

COSRX

19 g / 0.67 oz.